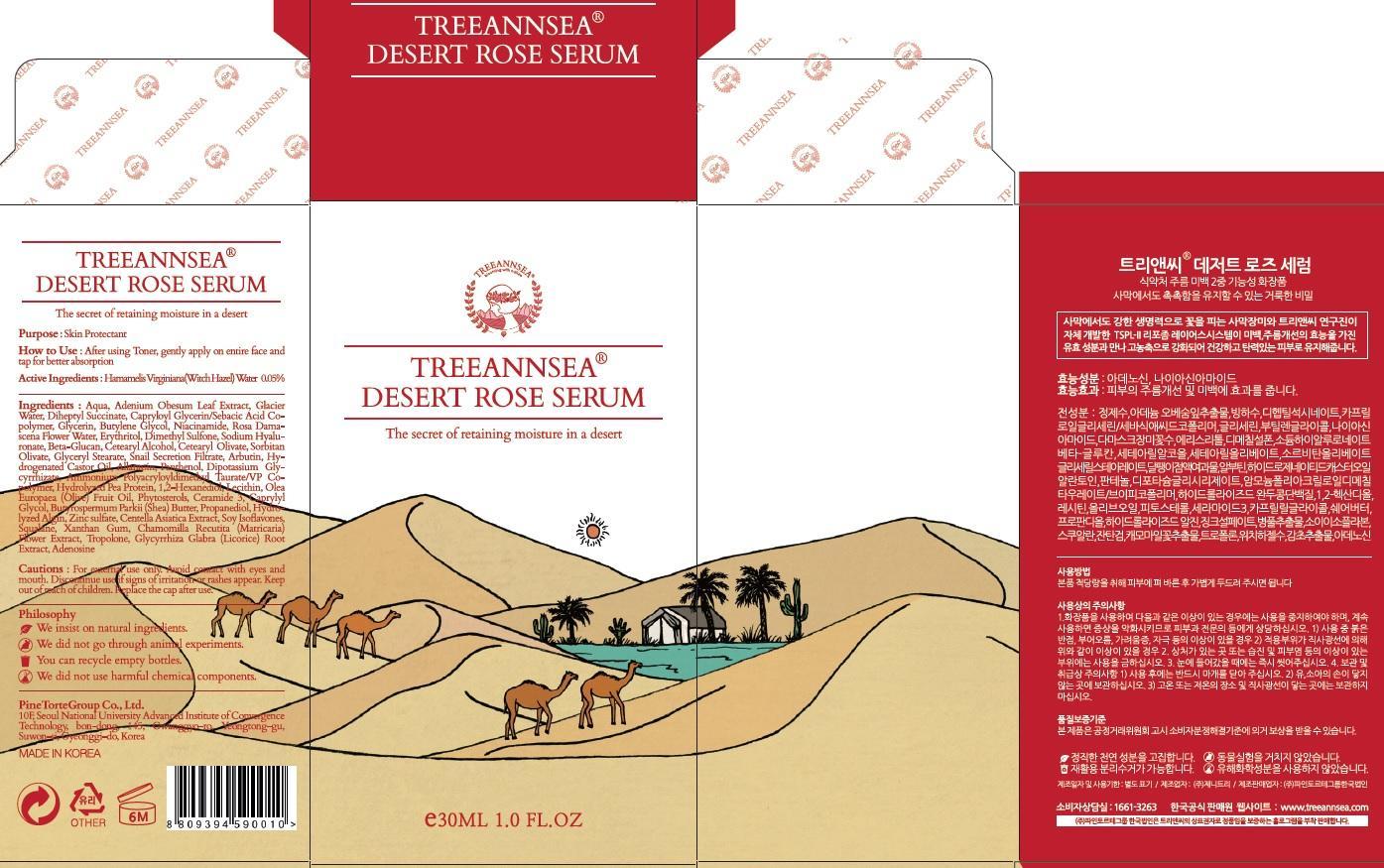 DRUG LABEL: TREEANNSEA DESERT ROSE SERUM
NDC: 69515-050 | Form: CREAM
Manufacturer: PINE TORTE GROUP CO., LTD.
Category: otc | Type: HUMAN OTC DRUG LABEL
Date: 20150319

ACTIVE INGREDIENTS: Witch Hazel 0.015 mg/30 mL
INACTIVE INGREDIENTS: WATER; Glycerin

ACTIVE INGREDIENT

Active Ingredients: Hamamelis Virginiana (Witch Hazel) Water 0.05%

INACTIVE INGREDIENT

Inactive Ingredients: Aqua, Adenium Obesum Leaf Extract, Glacier Water, Diheptyl Succinate, Capryloyl Glycerin/Sebacic Acid Copolymer, Glycerin, Butylene Glycol, Niacinamide, Rosa Damascena Flower Water, Erythritol, Dimethyl Sulfone, Sodium Hyaluronate, Beta-Glucan, Cetearyl Alcohol, Cetearyl Olivate, Sorbitan Olivate, Glyceryl Stearate, Snail Secretion Filtrate, Arbutin, Hydrogenated Castor Oil, Allantoin, Panthenol, Dipotassium Glycyrrhizate, Ammonium Polyacryloyldimethyl Taurate/VP Copolymer, Hydrolyzed Pea Protein, 1,2-Hexanediol, Lecithin, Olea Europaea (Olive) Fruit Oil, Phytosterols, Ceramide 3, Caprylyl Glycol, Butyrospermum Parkii (Shea) Butter, Propanediol, Hydrolyzed Algin, Zinc sulfate, Centella Asiatica Extract, Soy Isoflavones, Squalane, Xanthan Gum , Chamomilla Recutita (Matricaria) Flower Extract, Tropolone, Glycyrrhiza Glabra (Licorice) Root Extract, Adenosine

PURPOSE

Purpose: Skin Protectant

Cautions

Cautions: For external use only. Avoid contact with eyes and mouth. Discountinue use if signs of irritation or rashes appear. Keep out of reach of children. Replace the cap after use.

KEEP OUT OF REACH OF CHILDREN

INDICATIONS & USAGE

How to use: After using Toner, gently apply on entire face and tap for better absorption.

DOSAGE & ADMINISTRATION

How to use: After using Toner, gently apply on entire face and tap for better absorption.